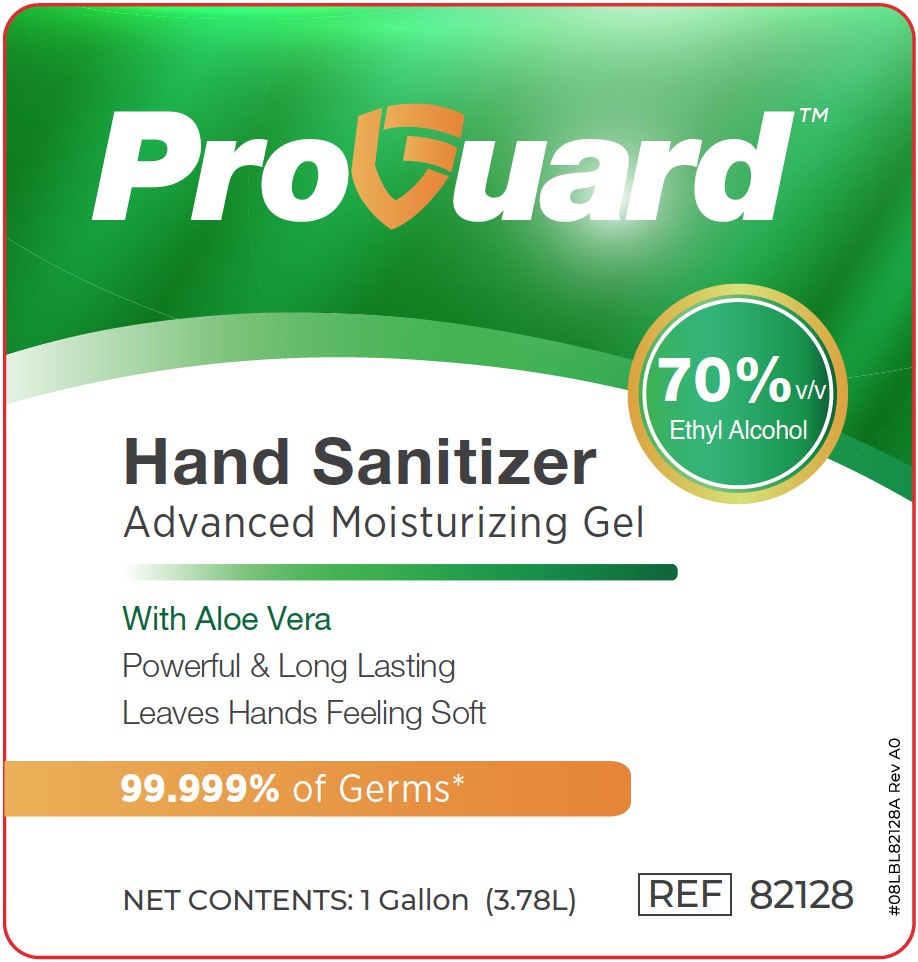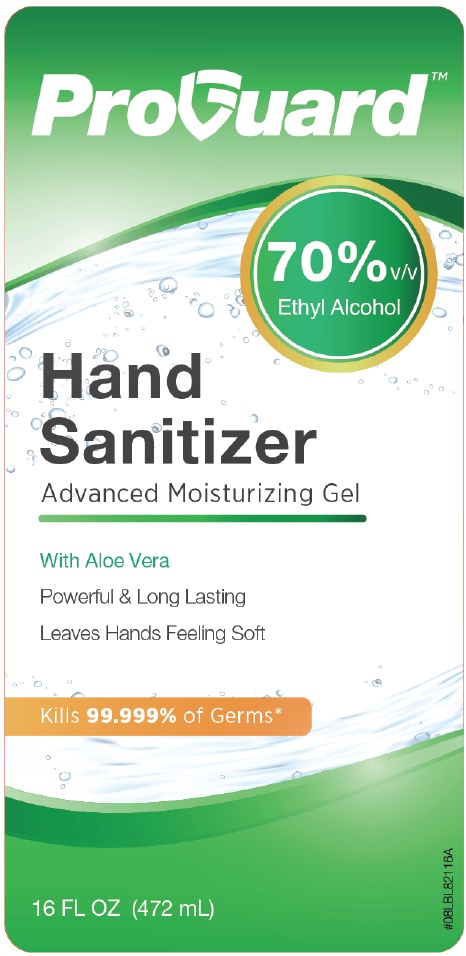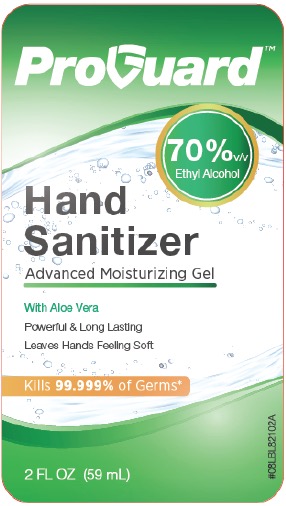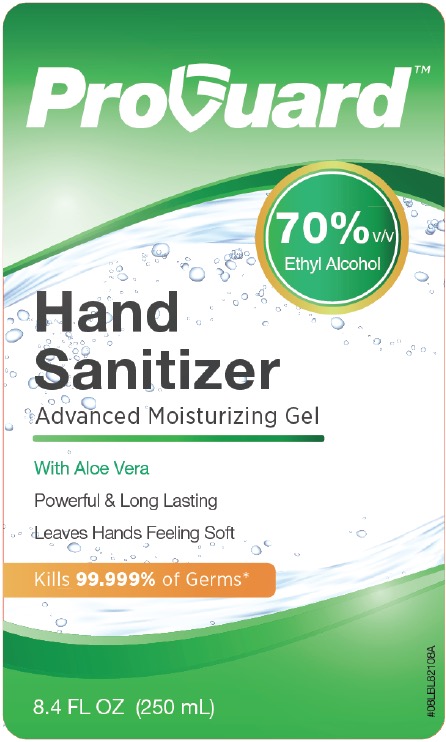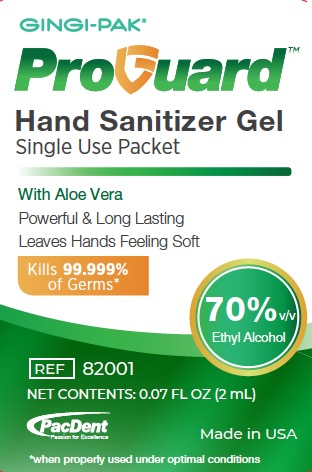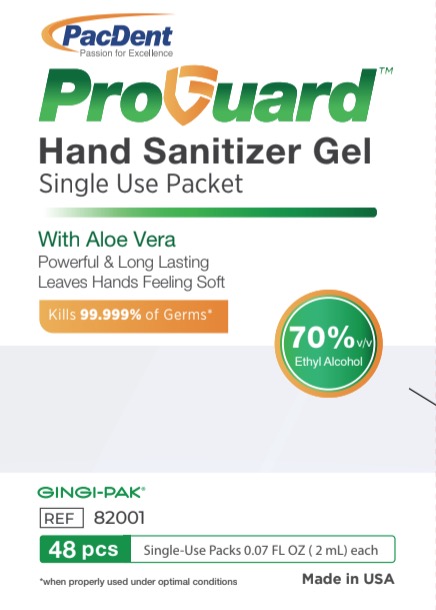 DRUG LABEL: ProGuard Hand Sanitizer Gel
NDC: 10129-081 | Form: GEL
Manufacturer: Gingi-Pak, a division of Belport Co.
Category: otc | Type: HUMAN OTC DRUG LABEL
Date: 20200810

ACTIVE INGREDIENTS: ALCOHOL 70 mL/100 mL
INACTIVE INGREDIENTS: SULISOBENZONE 0.05 g/100 mL; WATER 29 mL/100 mL; GLYCERIN 0.5 mL/100 mL; AMINOMETHYLPROPANOL 0.16 g/100 mL; ALOE VERA LEAF 0.5 mL/100 mL; CARBOMER HOMOPOLYMER, UNSPECIFIED TYPE 0.32 g/100 mL

ProGuard Hand Sanitizer Gel, 70%

Active Ingredient

Ethyl Alcohol 70% v/v. Purpose: Antiseptic

Purpose

Antiseptic

Use

- Reduce bacteria that potentially can cause disease.
- Recommened for repeated use.

Warnings

For external use only: hands. Flammable. Keep away from heat or flame.

Do Not Use

- around eyes
- in children less than 2 month of age
- on open skin wounds

When Using This Product

- Keep out of eyes, ears, and mouth. In case of contact with eyes, flush thoroughly with water.
- Avoid contact with broken skin.
- Do not inhale or ingest.

Keep out of reach of children.

If swallowed, get medical help or contact a Poison Control Center right away.

Directions

- Dispense enough gel in your palm to cover all surfaces of hands and finger. Rub hands together vigorously until dry.
- Usage on children requires adult supervision, not recommended for infants.
- Work best on clean and dry hands.

Other Information

- Store below 43 C (110F)
- May discolor certain fabrics or surfaces

Inactive Ingredients

Distilled Water, Glycerin, Carbomer 940, Benzophenone-4, Aloe Vera, Aminomethyl Propanol.